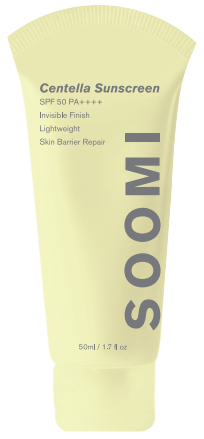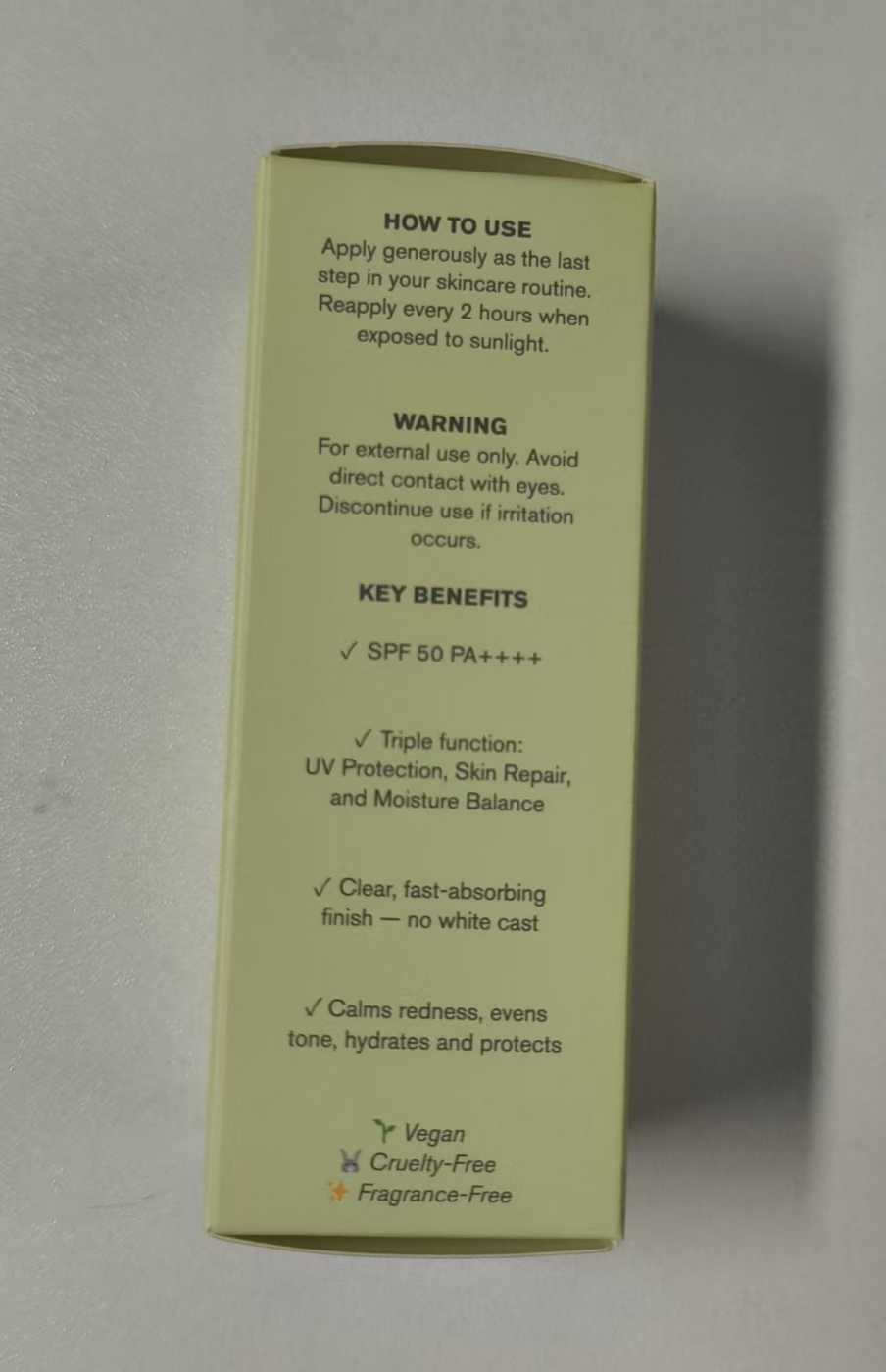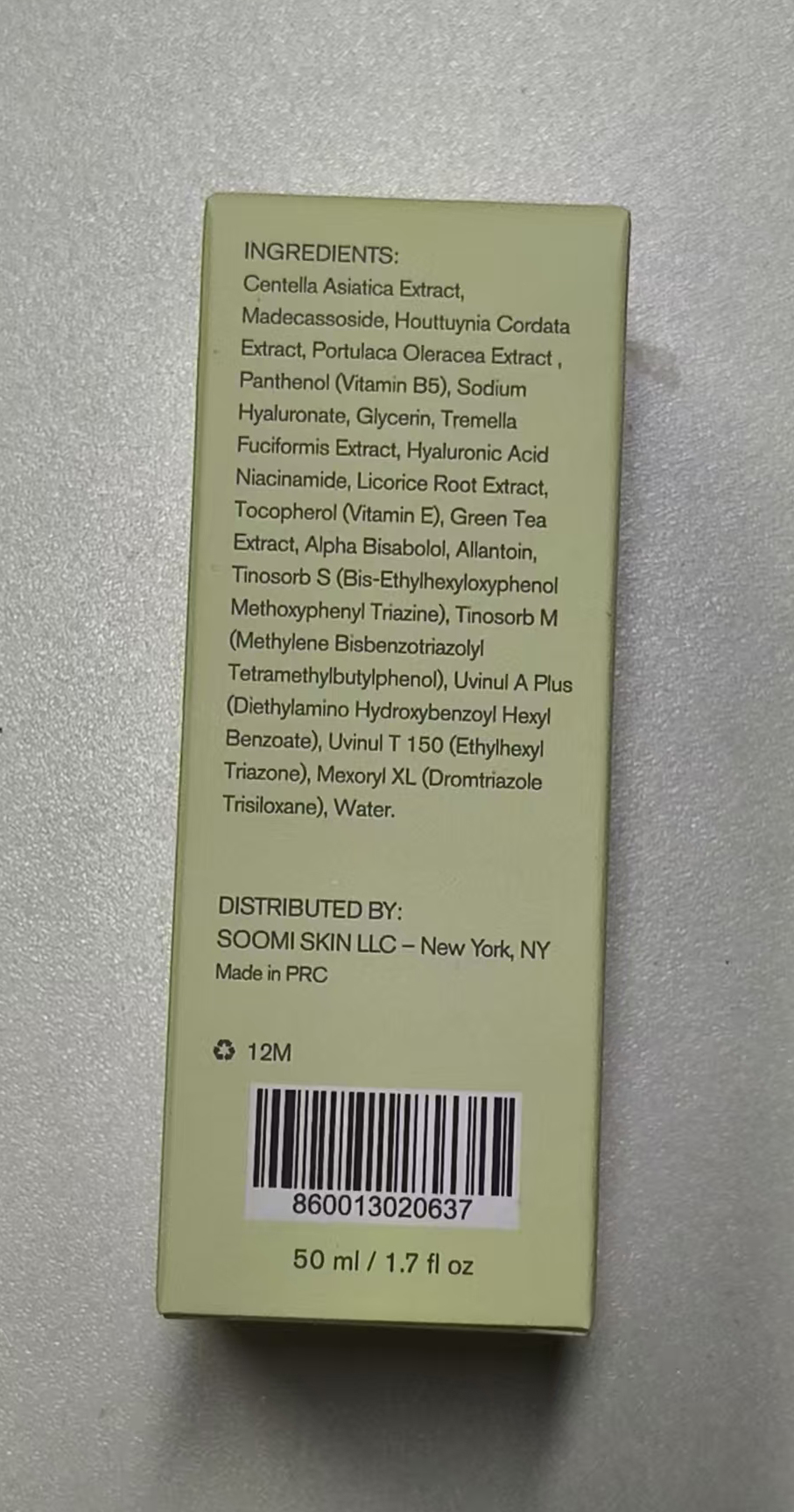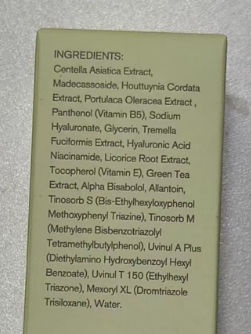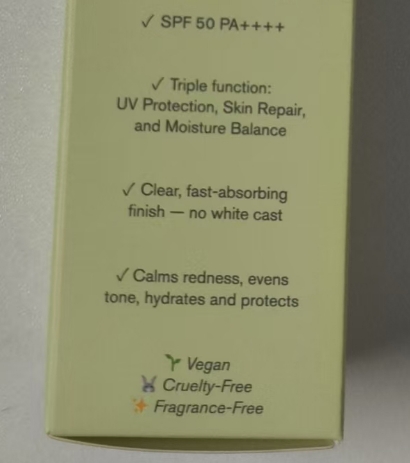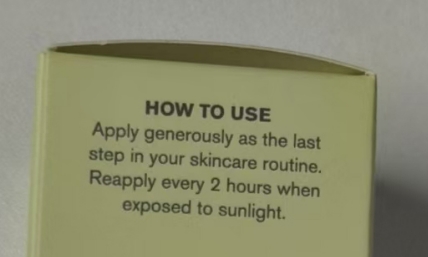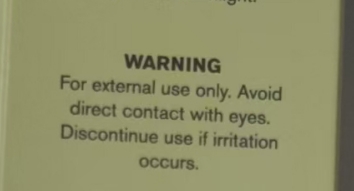 DRUG LABEL: Centella Sunscreen SPF 50
NDC: 85473-442 | Form: CREAM
Manufacturer: Guangzhou Yueyou Biological Technology Co., Ltd.
Category: otc | Type: HUMAN OTC DRUG LABEL
Date: 20250715

ACTIVE INGREDIENTS: DROMETRIZOLE TRISILOXANE 0.75 g/50 g; METHYLENE BIS-BENZOTRIAZOLYL TETRAMETHYLBUTYLPHENOL 1.5 g/50 g; BIS-ETHYLHEXYLOXYPHENOL METHOXYPHENYL TRIAZINE 1.5 g/50 g; DIETHYLAMINO HYDROXYBENZOYL HEXYL BENZOATE 1 g/50 g; ETHYLHEXYL TRIAZONE 1.75 g/50 g
INACTIVE INGREDIENTS: SODIUM HYALURONATE; MADECASSOSIDE; LICORICE; GREEN TEA LEAF; TREMELLA FUCIFORMIS FRUITING BODY; WATER; TOCOPHEROL; CENTELLA ASIATICA LEAF; HOUTTUYNIA CORDATA FLOWERING TOP; GLYCERIN; NIACINAMIDE; PANTHENOL; ALLANTOIN; PORTULACA OLERACEA LEAF; HYALURONIC ACID; .ALPHA.-BISABOLOL, (+)-

Centella Sunscreen SPF 50

Apply generously as the laststep in your skincare routine.Reapply every 2 hours when
exposed to sunlight.

WARNING

For external use only. Avoid direct contact with eyes. Discontinue use if irritation occurs.

INACTIVE INGREDIENT

Usage

how to use

Apply generously as the laststep in your skincare routineReapply every 2 hours whenexposed to sunlight.

KEEP OUT OF REACH OF CHILDREN